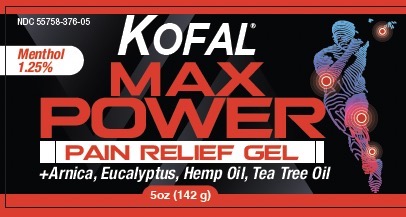 DRUG LABEL: Kofal
NDC: 55758-376 | Form: OINTMENT
Manufacturer: Pharmadel LLC
Category: otc | Type: HUMAN OTC DRUG LABEL
Date: 20251204

ACTIVE INGREDIENTS: MENTHOL, UNSPECIFIED FORM 1.25 g/100 g
INACTIVE INGREDIENTS: NONOXYNOL-9; POLYSORBATE 20; TEA TREE OIL; DMDM HYDANTOIN; ISOPROPYL ALCOHOL; CAMPHOR (SYNTHETIC); ARNICA MONTANA FLOWER; CARBOMER 940; WATER; ALCOHOL; EUCALYPTUS OIL; CANNABIS SATIVA SEED OIL; TROLAMINE; PROPYLENE GLYCOL

Kofal Max Power Menthol 1.25% (WP) (DA)

Active ingredient & Purpose

Active ingredient | Purpose
Menthol 1.25% .................. | External analgesic

Uses

For the temporary relief of minor aches and pains of muscles and joints associated with:

- simple backache
- arthritis
- strains
- bruises
- sprains

Warnings

For external use only. Avoid contact with the eyes.

Do not

- apply on wounds or irritated skin
- bandage tightly

Stop use and ask doctor immediately if

- condition worsens
- symptoms persist for more than 7 days or clear up and occur again within a few days

If pregnant or breast-feeding,

ask a health care professional before use.

Keep out of reach of children.

If swallowed get medical help, or contact a Poison Control Center immediately.

Directions

- adults and children 12 years of age and older: apply to affected area not more than 3 to 4 times daily
- children under 12 years of age: do not use, consult a doctor

Other information

- store between 59°- 86°F (15 - 30°C)
- do not use if clear seal over jar is broken, torn or missing

Inactive ingredients

alcohol, arnica montana flower, cannabis sativa (hemp) seed oil, camphor, carbomer 940, DMDM hydantoin, eucalyptus oil, isopropyl alcohol, nonoxynol-9, polysorbate 20, propylene glycol, tea tree oil, trolamine, water

Distributed by:

Pharmadel LLC

New Castle, DE 19720

+1-866-359-3478